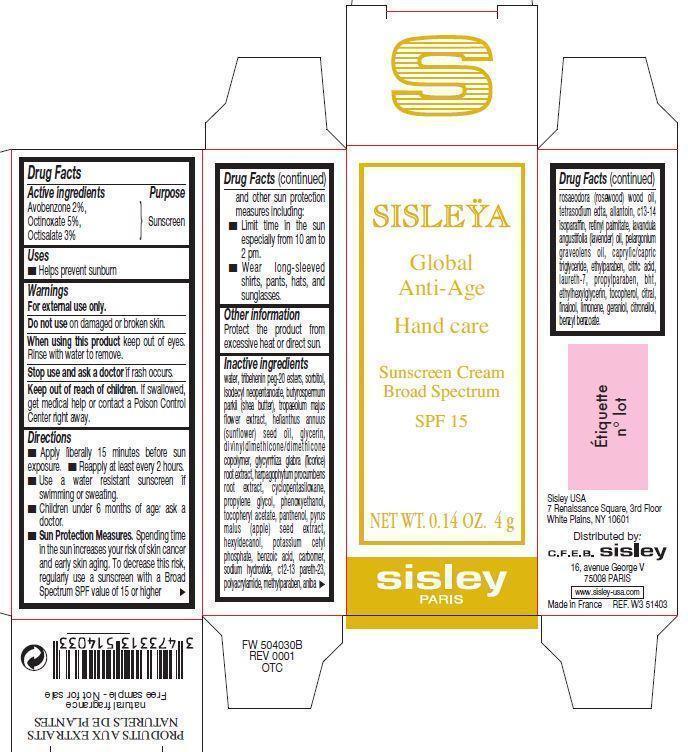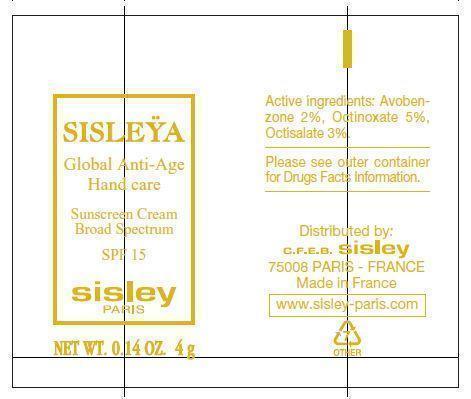 DRUG LABEL: SISLEYA Global Anti-Age Hand care
NDC: 66097-001 | Form: CREAM
Manufacturer: C.F.E.B. Sisley
Category: otc | Type: HUMAN OTC DRUG LABEL
Date: 20241210

ACTIVE INGREDIENTS: AVOBENZONE 20 mg/1 g; OCTINOXATE 50 mg/1 g; OCTISALATE 30 mg/1 g
INACTIVE INGREDIENTS: WATER; TRIBEHENIN PEG-20 ESTERS; SORBITOL; ISODECYL NEOPENTANOATE; SHEANUT OIL; TROPAEOLUM MAJUS FLOWER; SUNFLOWER OIL; GLYCERIN; GLYCYRRHIZA GLABRA; HARPAGOPHYTUM PROCUMBENS ROOT; CYCLOMETHICONE 5; PROPYLENE GLYCOL; PHENOXYETHANOL; .ALPHA.-TOCOPHEROL ACETATE; PANTHENOL; APPLE SEED; HEXYLDECANOL; POTASSIUM CETYL PHOSPHATE; BENZOIC ACID; SODIUM HYDROXIDE; C12-13 PARETH-23; METHYLPARABEN; ROSEWOOD OIL; EDETATE SODIUM; ALLANTOIN; C13-14 ISOPARAFFIN; VITAMIN A PALMITATE; LAVENDER OIL; GERANIUM OIL, ALGERIAN TYPE; MEDIUM-CHAIN TRIGLYCERIDES; ETHYLPARABEN; CITRIC ACID MONOHYDRATE; LAURETH-7; PROPYLPARABEN; BUTYLATED HYDROXYTOLUENE; ETHYLHEXYLGLYCERIN; TOCOPHEROL; CITRAL; LINALOOL, (+/-)-; GERANIOL; .BETA.-CITRONELLOL, (R)-; BENZYL BENZOATE

SISLEYA Global Anti-Age Hand care SPF 15

Active Ingredients

Avobenzone 2% Octinoxate 5% Octisalate 3%

Purpose

Sunscreen

Uses

- Helps prevent sunburn

Warnings

For external use only.

Do not use

on damaged or broken skin.

When using this product

keep out of eyes. Rinse with water to remove.

Stop use and ask a doctor

if rash occurs.

Keep out of reach of children.

If swallowed, get medical help or contact a Poison Control Center right away.

Directions

- Apply liberally 15 minutes before sun exposure.
- Reapply at least every 2 hours.
- Use a water resistant sunscreen if swimming or sweating.
- Children under 6 months of age: ask a doctor
- Spending time in the sun increases our risk of skin cancer and early skin aging. To decrease this risk, regularly use a sunscreen with a Broad spectrum SPF value of 15 or higher and other sun protection measures including: Sun Protection Measures.
- Limit time in the sun especially from 10 am to 2 pm
- Wear long-sleeved shirts, pants, hats and sunglasses.

Other information

Protect the product from excessive heat or direct sun.

Inactive ingredients

water, tribehenin peg-20 esters, sorbitol, isodecyl neopentanoate, butyrospermum parkii (shea butter), tropaeolum majus flower extract, helianthus annuus (sunflower) seed oil, glycyrrhiza glabra (licorice) root extract, harpagophytum procumbens root extract, cyclopentasiloxane, propylene glycol, phenoxyethanol, tocopheryl acetate, panthenol, pyrus malus (apple) seed extract, hexyldecanol, potassium cetyl phosphate, benzoic acid, sodium hydroxide, c12-13 pareth-23, methylparaben, aniba rosaeodora (rosewood) wood oil,edetate sodium, allantoin, c13-14 isoparaffin, retinyl palmitate, lavandula angustifolia (lavender) oil, pelargonium graveolens oil, caprylic/capric triglyceride, ethylparaben, citric acid, laureth-7, propylparaben, bht, ethylhexylglycerin, tocopherol, linalool, limonene, geraniol, citronellol, benzyl benzoate

PACKAGE LABEL

SISLEYA Global Anti-Age Hand care Sunscreen Cream Broad Spectrum SPF 15 NET WT. 0.14 OZ. 4 g sisley PARIS Sisley USA 7 Renaissance Square, 3rd Floor, White Plains, NY 10601 Distributed by: C.F.E.B. sisley 16, avenue George V 75008 PARIS www.sisley-usa.com Made in France